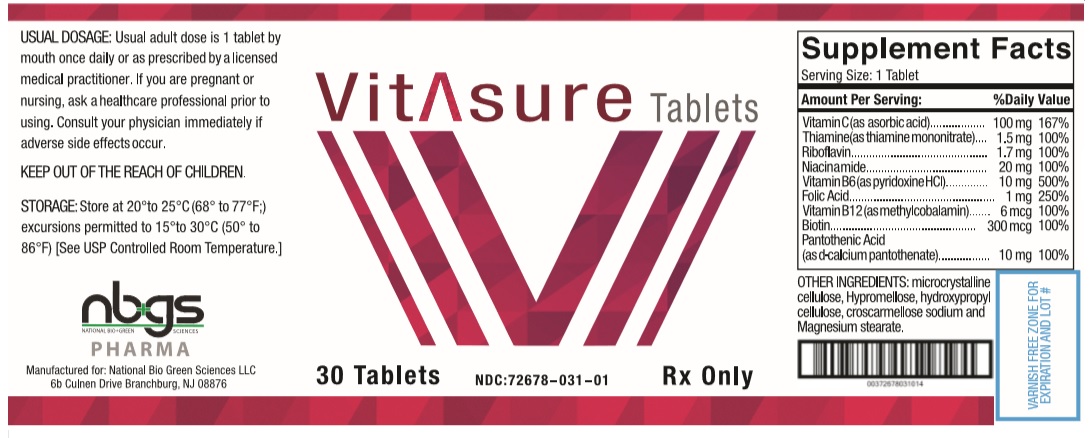 DRUG LABEL: VITASURE
NDC: 72678-031 | Form: TABLET, COATED
Manufacturer: NATIONAL BIO GREEN SCIENCES LIMITED LIABILITY COMPANY
Category: other | Type: DIETARY SUPPLEMENT
Date: 20190702

ACTIVE INGREDIENTS: ASCORBIC ACID 100 mg/1 1; THIAMINE MONONITRATE 1.5 mg/1 1; RIBOFLAVIN 1.7 mg/1 1; NIACINAMIDE 20 mg/1 1; PYRIDOXINE HYDROCHLORIDE 10 mg/1 1; FOLIC ACID 1 mg/1 1; METHYLCOBALAMIN 6 ug/1 1; BIOTIN 300 ug/1 1; CALCIUM PANTOTHENATE 10 mg/1 1
INACTIVE INGREDIENTS: MICROCRYSTALLINE CELLULOSE; HYPROMELLOSE 2208 (100000 MPA.S); HYDROXYPROPYL CELLULOSE (1600000 WAMW); CROSCARMELLOSE SODIUM; MAGNESIUM STEARATE

VITASURE

VITASURE Tablets Dietary Supplement Dispensed by Prescription†

Supplement Facts Serving Size: 1 Tablet Serving per container: 30
Amount Per Serving |  | % Daily Value
Vitamin C (as ascorbic Acid) | 100 mg | 167%
Thiamine (as thiamine mononitrate) | 1.5 mg | 100%
Riboflavin | 1.7 mg | 100%
Niacin (as niacinamide) | 20 mg | 100%
Vitamin B6 (as pyridoxine HCl) | 10 mg | 500%
Folic Acid | 1 mg | 250%
Vitamin B12 (as methylcobalamin) | 6 mcg | 100%
Biotin | 300 mcg | 100%
Pantothenic Acid (as d-calcium pantothenate) | 10 mg | 100%

OTHER INGREDIENTS: microcrystalline cellulose, Hypromellose, hydroxypropyl cellulose, croscarmellose sodium and Magnesium stearate.

DESCRIPTION

VITASURE Tablets is an orally administered prescription vitamin formulation for the clinical dietary management of suboptimal nutritional status in patients where advanced folate supplementation is required and nutritional supplementation in physiologically stressful conditions for maintenance of good health is needed.

PRECAUTIONS

CONTRAINDICATIONS
This product is contraindicated in patients with known hypersensitivity to any of the ingredients.

PRECAUTIONS
This product is contraindicated in patients with a known hypersensitivity to any of the ingredients.

VITASURE Tablets should only be used under the direction and supervision of a licensed medical practitioner. Use with caution in patients that may have a medical condition, are pregnant, lactating, trying to conceive, under the age of 18, or taking medications.

Folic acid supplementation may obscure pernicious anemia, in that hematologic remission can occur while neurological manifestations progress.

Keep out of reach of children.

Pregnancy and Lactation:
VITASURE Tablets is not intended for use in pregnant or lactating patients

ADVERSE REACTIONS
Allergic sensitizations have been reported following oral administration of folic acid. Consult your physician immediately if adverse side effects occur.

DOSAGE AND ADMINISTRATION

Usual adult dose is 1 tablet by mouth once or twice daily or as prescribed by a licensed medical practitioner.

HOW SUPPLIED HEALTH CLAIM:

VITASURE Tablets are supplied as a small, round, 8.5 MM in size, yellow, with no scoring. VITASURE Tablets is available as the following:

72678-031-01* 30ct bottle

Store at 20° to 25°C (68° to 77°F; excursions permitted to 15° to 30°C (59° to 86°F) [See USP Controlled Room Temperature]

Manufactured for:
NBGS Pharma, LLC
Branchburg, NJ 08876

Call your doctor for medical advice about side effects. You may report side effects to NBGS Pharma, LLC at 1-908-255-4133.

*NBGS Pharma does not represent these product codes to be National Drug Codes (NDC). Product codes are formatted according to standard industry practice, to meet the formatting requirement by pedigree reporting and supply-chain control including pharmacies.

† This product is a prescription-folate with or without other dietary ingredients that – due to increased folate levels increased risk associated with masking of B12 deficiency (pernicious anemia) requires administration under the care of a licensed medical practitioner (61 FR 8760). The most appropriate way to ensure pedigree reporting consistent with these regulatory guidelines and safety monitoring is to dispense this product only by prescription (Rx). This is not an Orange Book product. This product may be administered only under a physician’s supervision and all prescriptions using this product shall be pursuant to state statutes as applicable. The ingredients, indication or claims of this product are not to be construed to be drug claims.